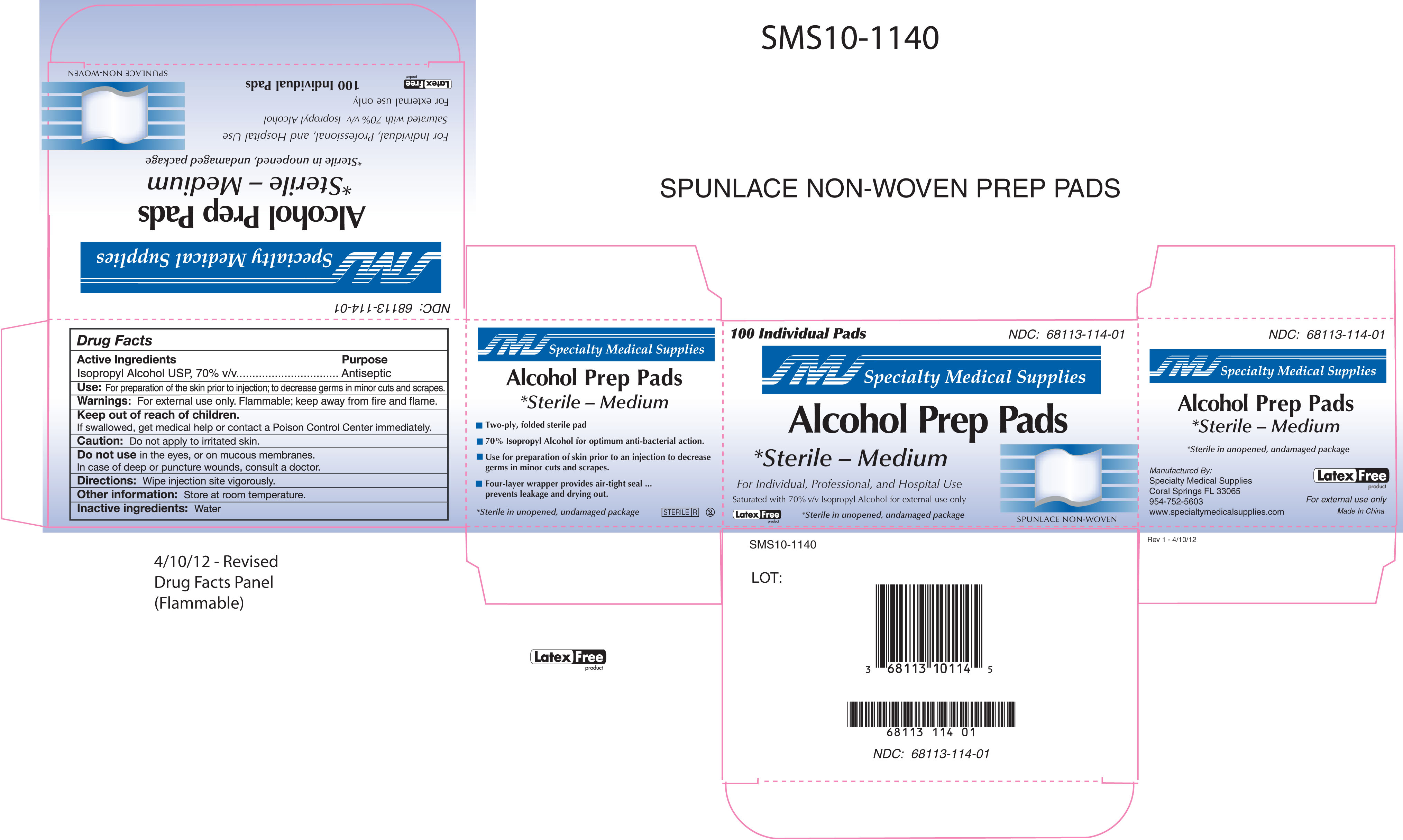 DRUG LABEL: Sterile Alcohol Prep Pads
NDC: 68113-114 | Form: LIQUID
Manufacturer: Carribbean Medical Brokers d.b.a. Specialty Medical Supplies
Category: otc | Type: HUMAN OTC DRUG LABEL
Date: 20120914

ACTIVE INGREDIENTS: ISOPROPYL ALCOHOL 0.8 g/1 mL
INACTIVE INGREDIENTS: WATER

Sterile Alcohol Prep Pad

Active Ingredients:

Isopropyl Alcohol USP, 70% v/v

Purpose

Antiseptic

Use

For preparation of skin prior to an injection to decrease germs in minor cuts and scrapes.

Warning

For external use only. Flammable, keep away from fire and flame

Keep out of reach of children

If swallowed, get medical help or contact a Poison Control Center right away.

Caution

Do not apply to irritated skin

Do not use in the eyes or on mucous membranes, in case of deep or puncture wounds, consult a doctor.

Directions

Wipe injection site vigorously.

Other Information

Store at room temperature.

Inactive Ingredient

Water

Manufactured by

Specialty Medical Supplies

Coral Springs, FL 33065

954-752-5603

www.specialtymedicalsupplies.com

Made in China

100 Individual Pads

NDC: 68113-114-01

Specialty Medical Supplies

Alcohol Prep Pads

Sterile - Medium

Antiseptic

For Individual, Professional, and Hospital Use

Saturated with 70% v/v Isopropyl Alcohol. For external use only

Sterile in unopened, undamaged package.

Latex Free